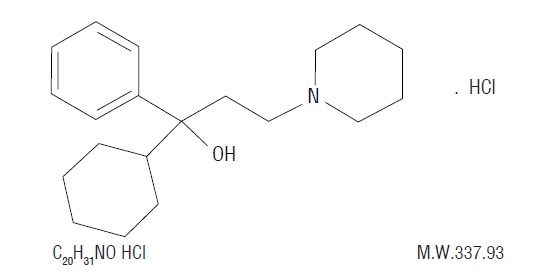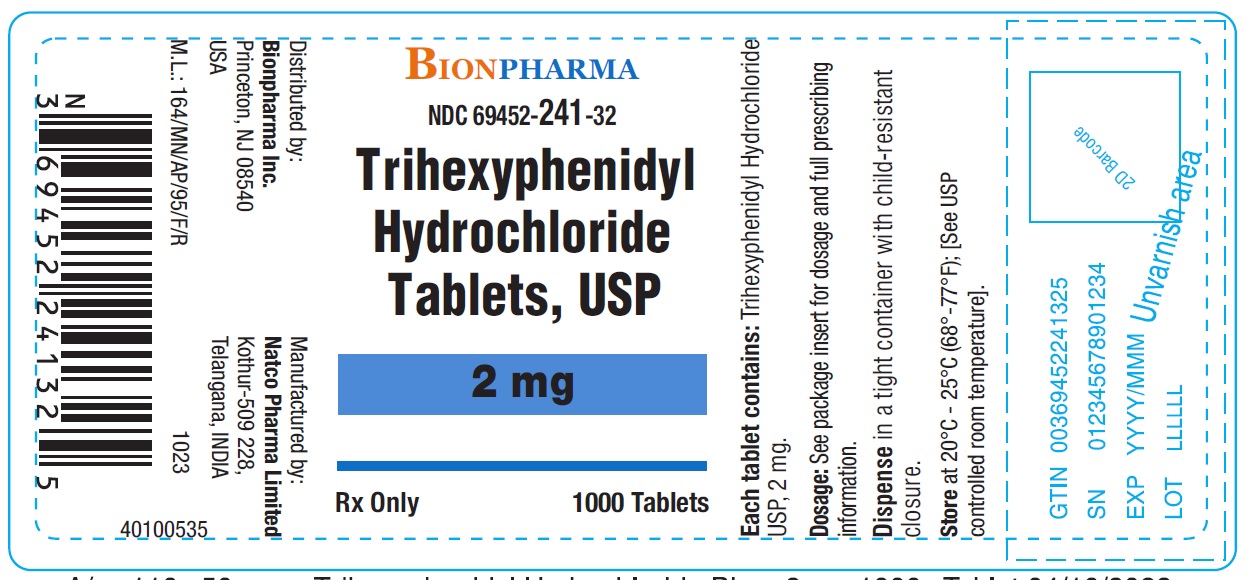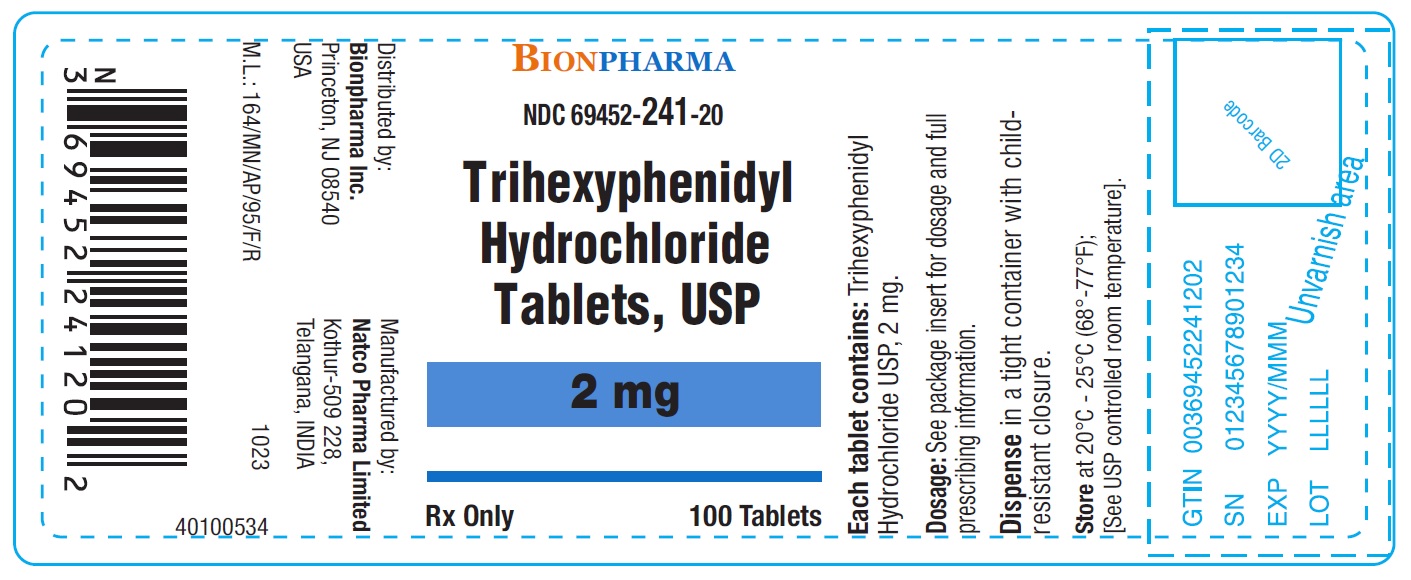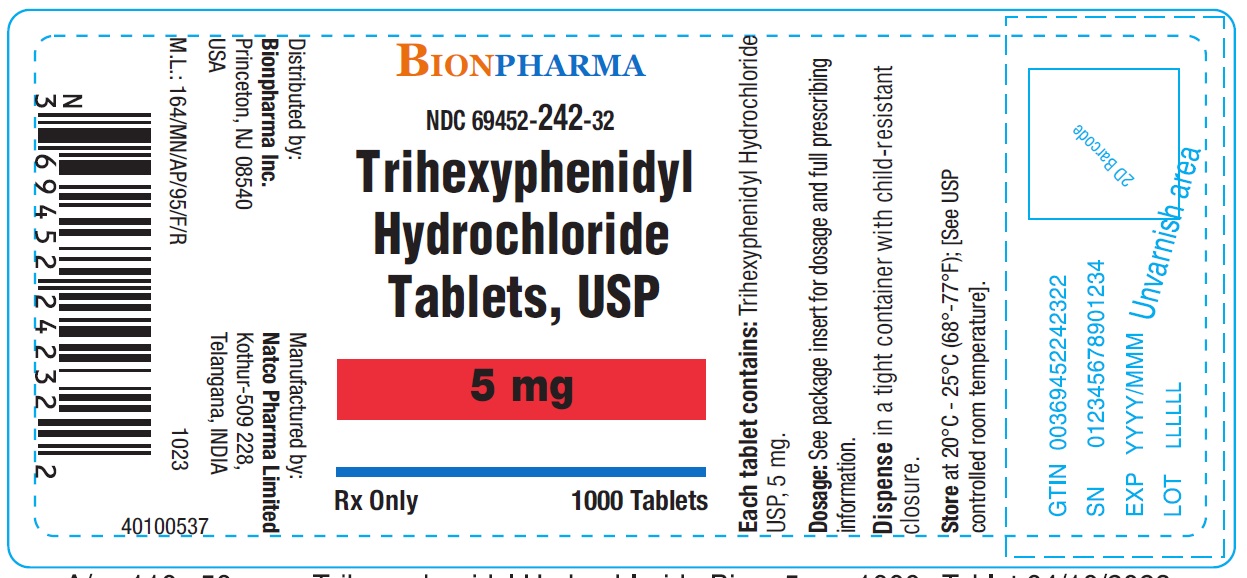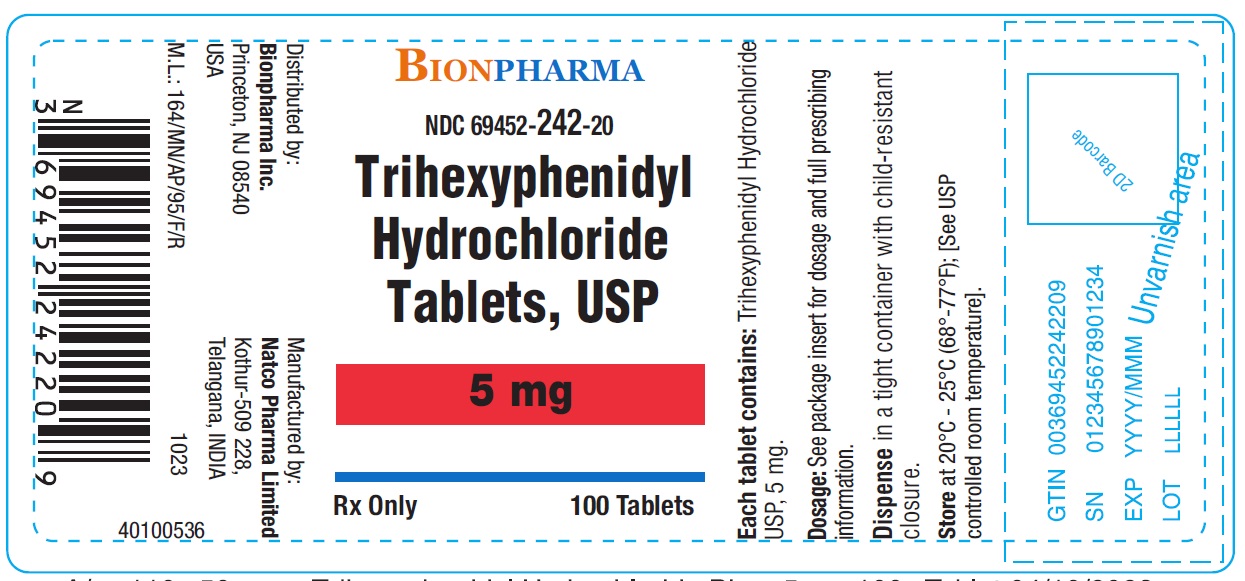 DRUG LABEL: Trihexyphenidyl Hydrochloride
NDC: 69452-241 | Form: TABLET
Manufacturer: Bionpharma Inc.
Category: prescription | Type: HUMAN PRESCRIPTION DRUG LABEL
Date: 20250702

ACTIVE INGREDIENTS: TRIHEXYPHENIDYL HYDROCHLORIDE 2 mg/1 1
INACTIVE INGREDIENTS: CELLULOSE, MICROCRYSTALLINE; MAGNESIUM STEARATE; SODIUM STARCH GLYCOLATE TYPE A POTATO

Rx Only

DESCRIPTION

Trihexyphenidyl HCl is a synthetic antispasmodic drug. It is designated chemically as α-Cyclohexylα-phenyl-1-piperidinepropanol hydrochloride and its structural formula is as follows:

Trihexyphenidyl HCl occurs as a white or creamy-white, almost odorless, crystalline powder. It is very slightly soluble in ether and benzene, slightly soluble in water and soluble in methanol.

Trihexyphenidyl Hydrochloride Tablets USP 2 mg and 5 mg contain the following inactive ingredients: magnesium stearate, microcrystalline cellulose and sodium starch glycolate.

CLINICAL PHARMACOLOGY

Trihexyphenidyl HCl exerts a direct inhibitory effect upon the parasympathetic nervous system. It also has a relaxing effect on smooth musculature; exerted both directly upon the muscle tissue itself and indirectly through an inhibitory effect upon the parasympathetic nervous system. Its therapeutic properties are similar to those of atropine although undesirable side effects are ordinarily less frequent and severe than with the latter.

INDICATIONS AND USAGE

Trihexyphenidyl HCl is indicated as an adjunct in the treatment of all forms of parkinsonism (postencephalitic, arteriosclerotic, and idiopathic). It is often useful as adjuvant therapy when treating these forms of parkinsonism with levodopa. Additionally, it is indicated for the control of extrapyramidal disorders caused by central nervous system drugs such as the dibenzoxazepines, phenothiazines, thioxanthenes, and butyrophenones.

CONTRAINDICATIONS

Trihexyphenidyl HCl is contraindicated in patients with hypersensitivity to trihexyphenidyl HCl or to any of the tablet ingredients. Trihexyphenidyl HCl is also contraindicated in patients with narrow angle glaucoma. Blindness after long-term use due to narrow angle glaucoma has been reported.

WARNINGS

Patients to be treated with trihexyphenidyl HCl should have a gonioscope evaluation prior to initiation of therapy and close monitoring of intraocular pressures. The use of anticholinergic drugs may precipitate angle closure with an increase in intraocular pressure. If blurring of vision occurs during therapy, the possibility of narrow angle glaucoma should be considered. Blindness has been reported due to aggravation of narrow angle glaucoma (see CONTRAINDICATIONSand ADVERSE REACTIONS).
Trihexyphenidyl HCl should be administered with caution in hot weather, especially when given concomitantly with other atropine-like drugs to the chronically ill, alcoholics, those who have central nervous system disease, or those who do manual labor in a hot environment. Anhidrosis may occur more readily when some disturbance of sweating already exists. If there is evidence of anhidrosis, the possibility of hyperthermia should be considered. Dosage should be decreased so that the ability to maintain body heat equilibrium via perspiration is not impaired. Severe anhidrosis and fatal hyperthermia have occurred with the use of anticholinergics under the conditions described above.

Neuroleptic Malignant Syndrome
A potentially fatal symptom complex sometimes referred to as Neuroleptic Malignant Syndrome (NMS) has been reported in association with dose reduction or Discontinuation of trihexyphenidyl. Clinical manifestations of NMS are hyperpyrexia, muscle rigidity, altered mental status and evidence of autonomic instability (irregular pulse or blood pressure, tachycardia, diaphoresis and cardiac dysrhythmias).

The diagnostic evaluation of patients with this syndrome is complicated. In arriving at a diagnosis, it is important to identify cases where the clinical presentation includes both serious medical illness (eg, pneumonia, systemic infection, etc.) and untreated or inadequately treated extrapyramidal signs and symptoms (EPS). Other important considerations in the differential diagnosis include central anticholinergic toxicity, heat stroke, drug fever, and primary central nervous system (CNS) pathology.

PRECAUTIONS

General

Patients with cardiac, liver, or kidney disorders, or with hypertension, should be closely monitored.

Since trihexyphenidyl HCl has atropine-like properties, patients on long-term treatment should be carefully monitored for untoward reactions.
Since trihexyphenidyl HCl has parasympatholytic activity, it should be used with caution in patients with glaucoma, obstructive disease of the gastrointestinal or genitourinary tracts, and in elderly males with possible prostatic hypertrophy. Incipient glaucoma may be precipitated by parasympatholytic drugs such as trihexyphenidyl HCl.

Tardive dyskinesia may appear in some patients on long-term therapy with antipsychotic drugs or may occur after therapy with these drugs has been discontinued. Antiparkinsonism agents do not alleviate the symptoms of tardive dyskinesia, and in some instances may aggravate them.

However, parkinsonism and tardive dyskinesia often coexist in patients receiving chronic neuroleptic treatment, and anticholinergic therapy with trihexyphenidyl HCl may relieve some of these parkinsonism symptoms. Trihexyphenidyl HCl is not recommended for use in patients with tardive dyskinesia unless they have concomitant Parkinson’s disease.

Patients with arteriosclerosis or with a history of idiosyncrasy to other drugs may exhibit reactions of mental confusion, agitation, disturbed behavior, or nausea and vomiting.Such patients should be allowed to develop a tolerance through the initial administration of a small dose and gradual increase in dose until an effective level is reached. If a severe reaction should occur, administration of the drug should be discontinued for a few days and then resumed at a lower dosage. Psychiatric disturbances can result from indiscriminate use (leading to overdosage) to sustain continued euphoria. (See DRUG ABUSE AND DEPENDENCE.)

Abrupt withdrawal of treatment for parkinsonism may result in acute exacerbation of parkinsonism symptoms; therefore, abrupt withdrawal should be avoided (see DOSAGE AND ADMINISTRATION).

Information for Patients

Trihexyphenidyl HCl may impair mental and/or physical abilities required for performance of hazardous tasks, such as operating machinery or driving a motor vehicle. Patients should be cautioned about operating machinery, including automobiles, until they are reasonably certain that trihexyphenidyl HCl therapy does not adversely affect their ability to engage in such activities.

Because of increased sedative effects, patients should be cautioned to avoid the use of alcohol or other CNS depressants while taking trihexyphenidyl HCl.

Since this medication may increase the susceptibility to heat stroke (gastrointestinal (GI) problems, fever, heat intolerance), use with caution during hot weather. (See WARNINGS.)

Patients should be advised to report the occurrence of Gl problems, fever, or heat intolerance promptly since paralytic ileus, hyperthermia, or heat stroke may occur.
If GI upset occurs, trihexyphenidyl HCl may be taken with food.
Patients should have close monitoring of intraocular pressure. (See WARNINGS.)

Drug Interactions

Cannabinoids, barbiturates, opiates, and alcohol may have additive effects with trihexyphenidyl HCl, and thus, an abuse potential exists.

Concurrent use of alcohol or other CNS depressants with trihexyphenidyl HCl may cause increased sedative effects.

Monoamine oxidase inhibitors and tricyclic antidepressants possessing significant anticholinergic activity may intensify the anticholinergic effects of antidyskinetic agents because of the secondary anticholinergic activities of these medications.

Prophylactic administration of anticholinergic agents, such as trihexyphenidyl, as a prevention of drug-induced parkinsonism during neuroleptic therapy is not recommended. There may be an increased risk for the development of tardive dyskinesia during concomitant administration of anticholinergics and neuroleptics (see PRECAUTIONS, General).

The usual dose of either trihexyphenidyl or levodopa may need to be reduced during concomitant therapy, since concomitant administration may increase drug-induced involuntary movements (see DOSAGE AND ADMINISTRATION).

Carcinogenesis, Mutagenesis, Impairment of Fertility

No carcinogenicity studies or adequate genotoxicity or fertility studies have been conducted for trihexyphenidyl HCl.

Pregnancy

TERATOGENIC EFFECTS PREGNANCY CATEGORY C
Animal reproduction studies to evaluate teratogenic and embryotoxic potential have not been conducted with trihexyphenidyl HCl. It is also not known whether trihexyphenidyl HCl can cause fetal harm when administered to a pregnant woman or can affect reproduction capacity. Trihexyphenidyl HCl should be given to a pregnant woman only if clearly needed.

Nursing Mothers

It is not known whether this drug is excreted in human milk. Because many drugs are excreted in human milk, caution should be exercised when trihexyphenidyl HCl is administered to a nursing woman.

As with other anticholinergics, trihexyphenidyl may cause suppression of lactation.Therefore, trihexyphenidyl should only be used if the expected benefit to the mother outweighs the potential risk to the infant.

Pediatric Use

Safety and effectiveness in pediatric patients have not been established. (See also ADVERSE REACTIONS.)

Geriatric Use

Sensitivity to the actions of parasympatholytic drugs may increase with age, particularly over the age of 60; therefore, elderly patients generally should be started on low doses of trihexyphenidyl HCl and observed closely. Trihexyphenidyl HCl has been shown to cause some cognitive dysfunctions in the elderly, including confusion and memory impairment. (See ADVERSE REACTIONSand DOSAGE AND ADMINISTRATION.)

ADVERSE REACTIONS

Minor side effects, such as dryness of the mouth, blurred vision, dizziness, mild nausea or nervousness, will be experienced by 30 to 50 percent of all patients. These sensations, however, are much less troublesome with trihexyphenidyl HCl than with belladonna alkaloids and are usually less disturbing than unalleviated parkinsonism.Such reactions tend to become less pronounced, and even to disappear, as treatment continues. Even before these reactions have remitted spontaneously, they may often be controlled by careful adjustment of dosage form, amount of drug, or interval between doses.

Isolated instances of suppurative parotitis secondary to excessive dryness of the mouth, skin rashes, dilatation of the colon, paralytic ileus, and certain psychiatric manifestations such as delusions, hallucinations, and paranoia, all of which may occur with any of the atropine-like drugs, have been reported rarely with trihexyphenidyl HCl.

Potential side effects associated with the use of any atropine-like drugs, including trihexyphenidyl HCl, include cognitive dysfunctions, including confusion and memory impairment; constipation, drowsiness, urinary hesitancy or retention, tachycardia, dilation of the pupil, increased intraocular pressure, choreiform movements, weakness, vomiting, and headache. Exacerbation of parkinsonism with abrupt treatment withdrawal has been reported. Neuroleptic malignant syndrome with abrupt treatment withdrawal has been reported (see WARNINGS, Neuroleptic Malignant Syndrome).

The occurrence of angle-closure glaucoma in patients receiving trihexyphenidyl HCl has been reported (blindness has been reported in some cases). Paradoxical sinus bradycardia, dry skin, and cycloplegia have been reported.

In addition to adverse events seen in adults, the following adverse events have been reported in the literature in pediatric patients: hyperkinesia, psychosis,forgetfulness, weight loss, restlessness, chorea, and sleep alterations.
To report SUSPECTED ADVERSE REACTIONS, contact Bionpharma Inc. at 1-888-235-BION or 1-888-235-2466 or FDA at 1-800-FDA-1088 orwww.fda.gov/medwatch

DRUG ABUSE AND DEPENDENCE

Although trihexyphenidyl HCl is not classified as a controlled substance, the possibility of abuse should be borne in mind due to its stimulant and euphoriant properties.

OVERDOSAGE

The mean oral LD50of trihexyphenidyl HCl has been reported to be 365 mg/kg (range, 325 to 410 mg/kg) in mice and 1660 mg/kg (1420 to 1940 mg/kg) in rats. At a dose of 40 mg/kg, dogs have exhibited emesis, restlessness followed by drowsiness, equilibrium disturbances, and mydriasis.

In humans, doses up to 300 mg (5 mg/kg) have been ingested without fatalities or sequelae. However, rare cases of death associated with trihexyphenidyl overdosages taken in conjunction with other CNS-depressant agents have been reported or in patients with a compromised respiratory condition. Trihexyphenidyl blood concentrations associated with the fatalities ranged from 0.03 to 0.80 mg/l.

Signs and Symptoms

Overdosage with trihexyphenidyl HCl produces typical central symptoms of atropine intoxication (the central anticholinergic syndrome). Correct diagnosis depends upon recognition of the peripheral signs of parasympathetic blockade, including dilated and sluggish pupils; warm, dry skin; facial flushing; decreased secretions of the mouth, pharynx, nose, and bronchi; foul-smelling breath; elevated temperature; tachycardia, cardiac arrhythmias; decreased bowel sounds; and urinary retention. Neuropsychiatric signs such as delirium, disorientation, anxiety, hallucinations, illusions, confusion, incoherence, agitation, hyperactivity, ataxia, lip smacking and tasting movements, loss of memory, paranoia, combativeness, and seizures may be present. The condition can progress to stupor, coma, paralysis, cardiac and respiratory arrest, and death.

Treatment

Treatment of acute overdose involves symptomatic and supportive therapy. Gastric lavage or other methods to limit absorption should be instituted. A small dose of diazepam or a short- acting barbiturate may be administered if CNS excitation is observed. Phenothiazines are contraindicated because the toxicity may be intensified due to their antimuscarinic action, causing coma. Respiratory support, artificial respiration or vasopressor agents may be necessary. Hyperpyrexia must be reversed, fluid volume replaced and acid-balance maintained. Urinary catheterization may be necessary. It is not known if trihexyphenidyl HCl is dialyzable.

DOSAGE AND ADMINISTRATION

Dosage should be individualized. The initial dose should be low and then increased gradually, especially in patients over 60 years of age. Whether trihexyphenidyl HCl may best be given before or after meals should be determined by the way the patient reacts. Postencephalitic patients, who are usually more prone to excessive salivation, may prefer to take it after meals and may, in addition, require small amounts of atropine which, under such circumstances, is sometimes an effective adjuvant. If trihexyphenidyl HCl tends to dry the mouth excessively, it may be better to take it before meals, unless it causes nausea. If taken after meals, the thirst sometimes induced can be allayed by mint candies, chewing gum or water.

Abrupt withdrawal of treatment for parkinsonism may result in acute exacerbation of parkinsonism symptoms; therefore, abrupt withdrawal should be avoided. Abrupt withdrawal of treatment may result in neuroleptic malignant syndrome (NMS) (see WARNINGS).

Idiopathic Parkinsonism

As initial therapy for parkinsonism, 1 mg of trihexyphenidyl HCl in tablet form may be administered the first day. The dose may then be increased by 2 mg increments at intervals of three to five days, until a total of 6 to 10 mg is given daily. The total daily dose will depend upon what is found to be the optimal level. Many patients derive maximum benefit from this daily total of 6 to 10 mg, but some patients, chiefly those in the postencephalitic group, may require a total daily dose of 12 to 15 mg.

Drug-Induced Parkinsonism

The size and frequency of the trihexyphenidyl HCl dose needed to control extrapyramidal reactions to commonly employed tranquilizers, notably the phenothiazines, thioxanthenes, and butyrophenones, must be determined empirically. The total daily dosage usually ranges between 5 and 15 mg although, in some cases, these reactions have been satisfactorily controlled with as little as 1 mg daily. It may be advisable to commence therapy with a single 1 mg dose. If the extrapyramidal manifestations are not controlled in a few hours, the subsequent doses may be progressively increased until satisfactory control is achieved. Satisfactory control may sometimes be more rapidly achieved by temporarily reducing the dosage of the tranquilizer when instituting trihexyphenidyl HCl therapy and then adjusting the dosage of both drugs until the desired ataractic effect is retained without onset of extrapyramidal reactions.

It is sometimes possible to maintain the patient on a reduced trihexyphenidyl HCl dosage after the reactions have remained under control for several days. Instances have been reported in which these reactions have remained in remission for long periods after trihexyphenidyl HCl therapy was discontinued.

Concomitant Use with Levodopa

When trihexyphenidyl HCl is used concomitantly with levodopa, the usual dose of each may need to be reduced. Careful adjustment is necessary, depending on side effects and degree of symptom control. An trihexyphenidyl HCl dosage of 3 to 6 mg daily, in divided doses, is usually adequate.

Concomitant Use with Other Parasympathetic Inhibitors

Trihexyphenidyl HCl may be substituted, in whole or in part, for other parasympathetic inhibitors. The usual technique is partial substitution initially, with progressive reduction in the other medication as the dose of trihexyphenidyl HCl is increased.

Trihexyphenidyl HCl tablets - The total daily intake of trihexyphenidyl HCl tablets is tolerated best if divided into 3 doses and taken at mealtimes. High doses (>10 mg daily) may be divided into 4 parts, with 3 doses administered at mealtimes and the fourth at bedtime.

HOW SUPPLIED

Trihexyphenidyl Hydrochloride Tablets, USP 2 mg are white colored, round debossed with N, T on either side of the score line and ‘2’ on the other side.

Trihexyphenidyl Hydrochloride Tablets, USP 2 mg are available in

Bottle of 100 tablets (NDC 69452-241-20)
Bottle of 1000 tablets (NDC 69452-241-32)
Trihexyphenidyl Hydrochloride Tablets, USP 5 mg are white colored, round debossed with N, T on either side of the score line and ‘5’ on other side.
Trihexyphenidyl Hydrochloride Tablets, USP 5 mg are available in
Bottle of 100 tablets (NDC 69452-242-20)
Bottle of 1000 tablets (NDC 69452-242-32)
Dispense in a tight container with child-resistant closure.
Store at 20°-25°C (68°- 77°F). [See USP controlled room temperature.]
Manufactured by:
NATCO PHARMA LIMITED
Kothur-509 228,
Telangana, India.
Distributed by:
Bionpharma Inc.
Princeton,
NJ 08540
USA

Trihexyphenidyl Hydrochloride Tablets USP 2 mg-Bottle of 100

NDC 69452-241-20
Each tablet contains Trihexyphenidyl hydrochloride USP 2 mg
Dispense in tight container with child-resistant closure.

Trihexyphenidyl Hydrochloride Tablets USP 2 mg-Bottle of 1000

NDC 69452-241-32
Each tablet contains Trihexyphenidyl hydrochloride USP 2 mg
Dispense in tight container with child-resistant closure.

Trihexyphenidyl Hydrochloride Tablets USP 5 mg-Bottle of 100

NDC 69452-242-20
Each tablet contains Trihexyphenidyl hydrochloride USP 5 mg
Dispense in tight container with child-resistant closure.

Trihexyphenidyl Hydrochloride Tablets USP 5 mg-Bottle of 1000

NDC 69452-242-32
Each tablet contains Trihexyphenidyl hydrochloride USP 5 mg
Dispense in tight container with child-resistant closure.